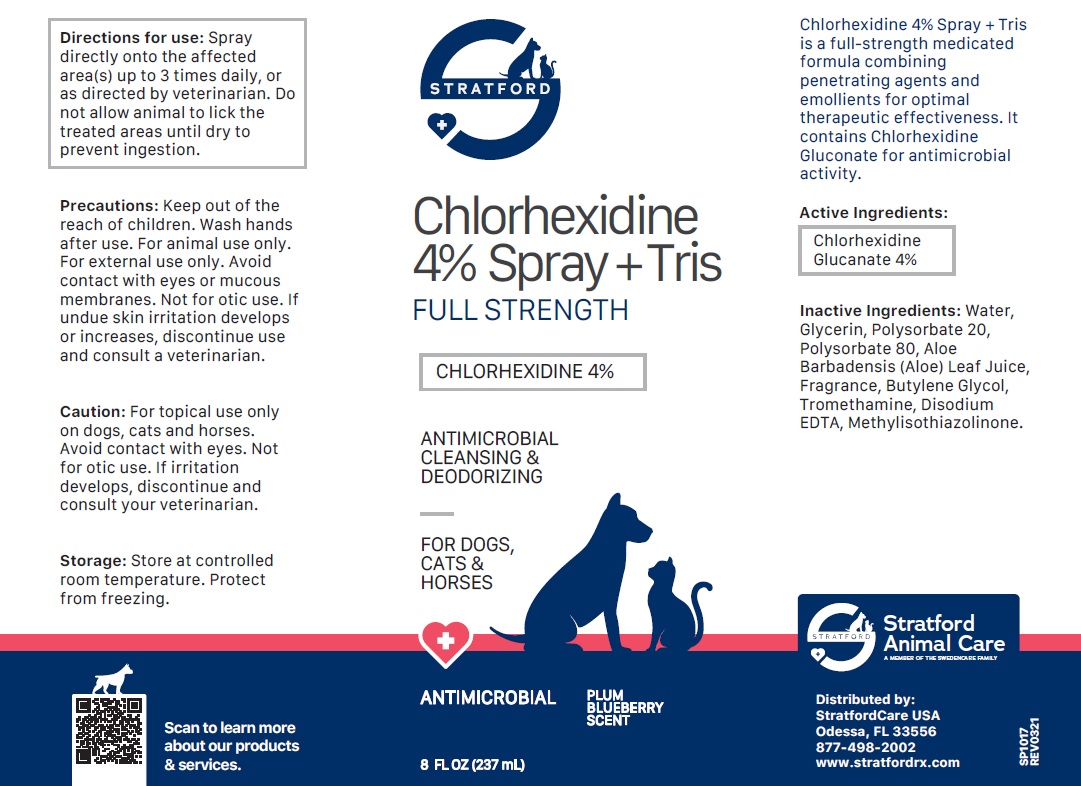 DRUG LABEL: Stratford Chlorhexidine 4% plus TRIS
NDC: 86069-118 | Form: SPRAY
Manufacturer: Stratford Care Usa, Inc.
Category: animal | Type: OTC ANIMAL DRUG LABEL
Date: 20221122

ACTIVE INGREDIENTS: CHLORHEXIDINE GLUCONATE 4 g/100 mL
INACTIVE INGREDIENTS: WATER; GLYCERIN; POLYSORBATE 20; POLYSORBATE 80; ALOE VERA LEAF; BUTYLENE GLYCOL; TROMETHAMINE; EDETATE DISODIUM ANHYDROUS; METHYLISOTHIAZOLINONE

Chlorhexidine 4% SPRAY + TRIS

Active Ingredients:

Chlorhexidine Gluconate 4%

PURPOSE

ANTIMICROBIAL

INDICATIONS AND USAGE

Chlorhexidine 4% Spray + Tris is a full-strength medicated formula combining penetrating agents and emollients for optimal therapeutic effectiveness. It contains Chlorhexidine Gluconate for antimicrobial activity.

INACTIVE INGREDIENT

Inactive Ingredients: Water, Glycerin, Polysorbate 20, Polysorbate 80, Aloe Barbadensis (Aloe) Leaf Juice, Fragrance, Butylene Glycol, Tromethamine, Disodium EDTA, Methylisothiazolinone.

DOSAGE AND ADMINISTRATION

Directions for use: Spray directly onto the affected area(s) up to 3 times daily, or as directed by veterinarian. Do not allow animal to lick the treated areas until dry to prevent ingestion.

PRECAUTIONS

Precautions: Keep out of the reach of children. Wash hands after use. For animal use only. For external use only. Avoid contact with eyes or mucous membranes. Not for otic use. If undue skin irritation develops or increases, discontinue use and consult a veterinarian.

Caution: For topical use only on dogs, cats and horses. Avoid contact with eyes. Not for otic use. If irritation develops, discontinue and consult your veterinarian.

STORAGE AND HANDLING

Storage: Store at controlled room temperature. Protect from freezing.

FULL STRENGTH

ANTIMICROBIAL CLEANSING & DEODORIZING

FOR DOGS, CATS & HORSES

PLUM BLUEBERRY SCENT

Stratford Animal Care
A MEMBER OF THE SWEDENCARE FAMILY

Distributed by:
StratfordCare USA
Odessa, FL 33556
877-498-2002
www.stratfordrx.com